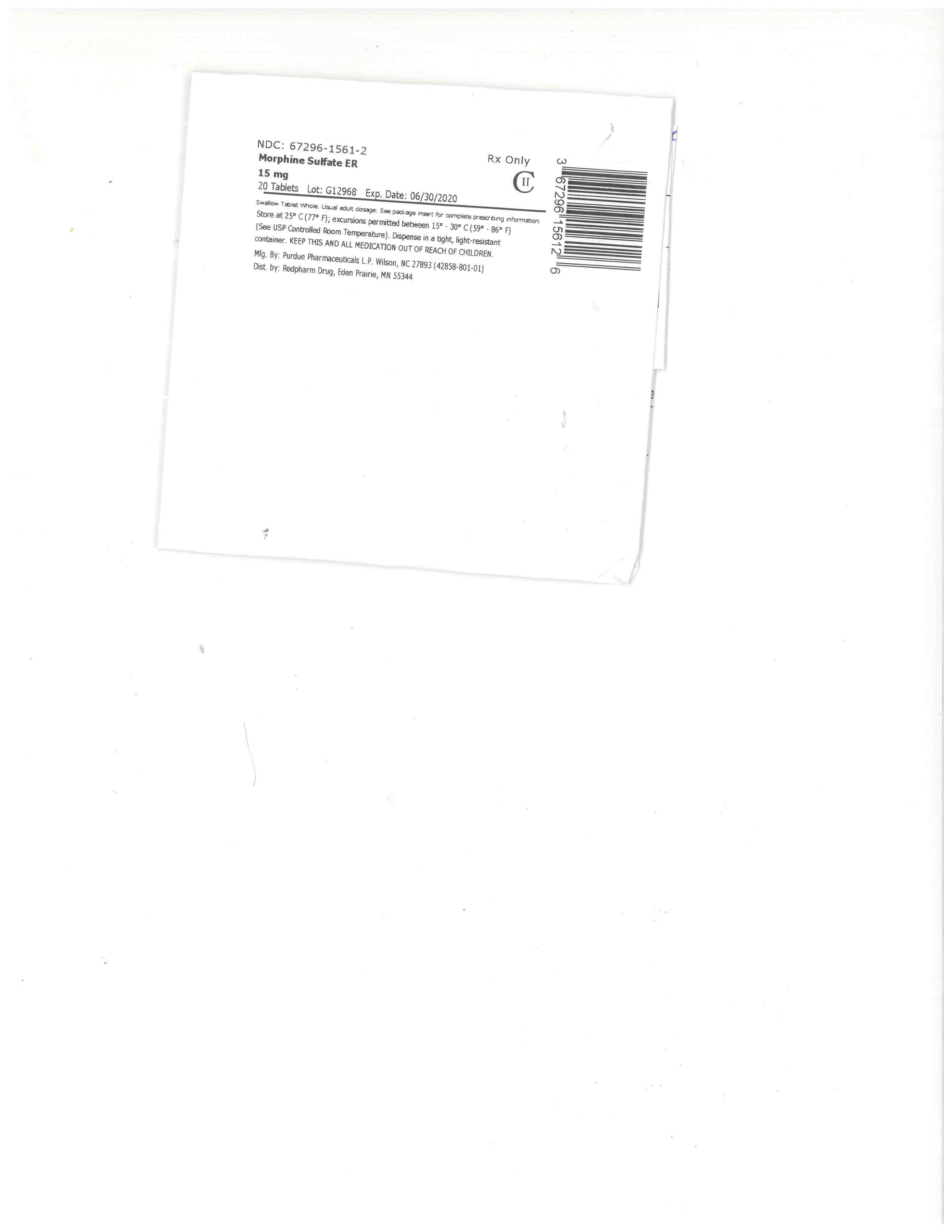 DRUG LABEL: Morphine Sulfate
NDC: 67296-1561 | Form: TABLET, FILM COATED, EXTENDED RELEASE
Manufacturer: RedPharm Drug, Inc.
Category: prescription | Type: HUMAN PRESCRIPTION DRUG LABEL
Date: 20220121
DEA Schedule: CII

ACTIVE INGREDIENTS: MORPHINE SULFATE 15 mg/1 1
INACTIVE INGREDIENTS: HYPROMELLOSES; POLYETHYLENE GLYCOL, UNSPECIFIED; LACTOSE; HYDROXYETHYL CELLULOSE (140 CPS AT 5%); TALC; FD&C BLUE NO. 2; MAGNESIUM STEARATE; POLYSORBATE 80; CETOSTEARYL ALCOHOL; TITANIUM DIOXIDE

Morphine Sulf ER 15mg #20

BOXED WARNING

WARNING: ADDICTION, ABUSE, AND MISUSE; LIFE-THREATENING RESPIRATORY DEPRESSION; ACCIDENTAL INGESTION; AND NEONATAL OPIOID WITHDRAWAL SYNDROME

Addiction, Abuse, and Misuse

Morphine sulfate extended-release tablets expose patients and other users to the risks of opioid addiction, abuse, and misuse, which can lead to overdose and death. Assess each patient’s risk prior to prescribing morphine sulfate extended-release tablets, and monitor all patients regularly for the development of these behaviors and conditions [see Warnings and Precautions (5.1)].

Life-Threatening Respiratory Depression
Serious, life-threatening, or fatal respiratory depression may occur with use of morphine sulfate extended-release tablets. Monitor for respiratory depression, especially during initiation of morphine sulfate extended-release tablets or following a dose increase. Instruct patients to swallow morphine sulfate extended-release tablets whole; crushing, chewing, or dissolving morphine sulfate extended-release tablets can cause rapid release and absorption of a potentially fatal dose of morphine [see Warnings and Precautions (5.2)].

Accidental Ingestion
Accidental ingestion of even one dose of morphine sulfate extended-release tablets, especially by children, can result in a fatal overdose of morphine [see Warnings and Precautions (5.2)].

Neonatal Opioid Withdrawal Syndrome
Prolonged use of morphine sulfate extended-release tablets during pregnancy can result in neonatal opioid withdrawal syndrome, which may be life-threatening if not recognized and treated, and requires management according to protocols developed by neonatology experts. If opioid use is required for a prolonged period in a pregnant woman, advise the patient of the risk of neonatal opioid withdrawal syndrome and ensure that appropriate treatment will be available [see Warnings and Precautions (5.3)].

HIGHLIGHTS OF PRESCRIBING INFORMATION

These highlights do not include all the information needed to use morphine sulfate extended-release tablets safely and effectively. See full prescribing information for morphine sulfate extended-release tablets.
MORPHINE sulfate extended-release tablets for oral use, CII
Initial U.S. Approval: 1941

WARNING: ADDICTION, ABUSE, AND MISUSE; LIFE-THREATENING RESPIRATORY DEPRESSION; ACCIDENTAL INGESTION; AND NEONATAL OPIOID WITHDRAWAL SYNDROME
SEE FULL PRESCRIBING INFORMATION FOR COMPLETE BOXED WARNING.

Morphine sulfate extended-release tablets expose users to risks of addiction, abuse, and misuse, which can lead to overdose and death. Assess each patient's risk before prescribing, and monitor regularly for development of these behaviors and conditions. (5.1)
Serious, life-threatening, or fatal respiratory depression may occur. Monitor closely, especially upon initiation or following a dose increase. Instruct patients to swallow morphine sulfate extended-release tablets whole to avoid exposure to a potentially fatal dose of morphine. (5.2)
Accidental ingestion of morphine sulfate extended-release tablets, especially in children, can result in fatal overdose of morphine. (5.2)
Prolonged use of morphine sulfate extended-release tablets during pregnancy can result in neonatal opioid withdrawal syndrome, which may be life-threatening if not recognized and treated. If opioid use is required for a prolonged period in a pregnant woman, advise the patient of the risk of neonatal opioid withdrawal syndrome and ensure that appropriate treatment will be available. (5.3)

RECENT MAJOR CHANGES

Boxed Warning 04/2014

Indications and Usage (1) 04/2014

Dosage and Administration (2) 04/2014

Warnings and Precautions (5) 04/2014

INDICATIONS AND USAGE

Morphine sulfate extended-release tablets are an opioid agonist product indicated for the management of pain severe enough to require daily, around-the-clock, long-term opioid treatment and for which alternative treatment options are inadequate. (1)

Limitations of Use

Because of the risks of addiction, abuse, and misuse with opioids, even at recommended doses, and because of the greater risks of overdose and death with extended-release opioid formulations, reserve morphine sulfate extended-release tablets for use in patients for whom alternative treatment options (e.g., non-opioid analgesics or immediate-release opioids) are ineffective, not tolerated, or would be otherwise inadequate to provide sufficient management of pain. (1)
Morphine sulfate extended-release tablets are not indicated as an as-needed (prn) analgesic. (1)

DOSAGE AND ADMINISTRATION

For opioid-naïve and opioid non-tolerant patients,initiate with 15 mg tablets orally every 8 to 12 hours. (2.1)
Do not abruptly discontinue morphine sulfate extended-release tablets in a physically dependent patient. (2.3)
Instruct patients to swallow morphine sulfate extended-release tablets intact. (2.4)

DOSAGE FORMS AND STRENGTHS

Extended-release tablets: 15 mg, 30 mg, 60 mg, 100 mg, 200 mg (3)

CONTRAINDICATIONS

Significant respiratory depression (4)
Acute or severe bronchial asthma (4)
Known or suspected paralytic ileus (4)
Hypersensitivity to morphine (4)

WARNINGS AND PRECAUTIONS

Interaction with CNS depressants: Concomitant use may cause profound sedation, respiratory depression, and death. If coadministration is required, consider dose reduction of one or both drugs because of additive pharmacologic effects.(5.4)
Elderly, cachectic, debilitated patients, and those with chronic pulmonary disease: Monitor closely because of increased risk for life-threatening respiratory depression. (5.5, 5.6)
Hypotensive effect: Monitor during dose initiation and titration. (5.7)
Patients with head injury or increased intracranial pressure: Monitor for sedation and respiratory depression. Avoid use of morphine sulfate extended-release tablets in patients with impaired consciousness or coma susceptible to intracranial effects of CO2 retention. (5.8)

ADVERSE REACTIONS

Most common adverse reactions: constipation, nausea, and sedation. (6.1)

To report SUSPECTED ADVERSE REACTIONS, contact Rhodes Pharmaceuticals L.P. at 1-888-827-0616 or FDA at 1-800-FDA-1088 or www.fda.gov/medwatch.

DRUG INTERACTIONS

Mixed agonist/antagonist and partial agonist opioid analgesics: Avoid use with morphine sulfate extended-release tablets because they may reduce analgesic effect of morphine sulfate extended-release tablets or precipitate withdrawal symptoms. (5.11, 7.2)
Monoamine oxidase inhibitors (MAOIs): Avoid morphine sulfate extended-release tablets in patients taking MAOIs or within 14 days of stopping such treatment. (7.4)

USE IN SPECIFIC POPULATIONS

Pregnancy: Based on animal data, may cause fetal harm. (8.1)
Nursing mothers: Morphine has been detected in human milk. Closely monitor infants of nursing women receiving morphine sulfate extended-release tablets. (8.3)

See 17 for PATIENT COUNSELING INFORMATION and Medication Guide.

Revised: 11/2016

FULL PRESCRIBING INFORMATION: CONTENTS*

WARNING: ADDICTION, ABUSE, AND MISUSE; LIFE-THREATENING RESPIRATORY DEPRESSION; ACCIDENTAL INGESTION; AND NEONATAL OPIOID WITHDRAWAL SYNDROME
1 INDICATIONS AND USAGE
2 DOSAGE AND ADMINISTRATION
2.1 Initial Dosing
2.2 Titration and Maintenance of Therapy
2.3 Discontinuation of Morphine Sulfate Extended-Release Tablets
2.4 Administration of Morphine Sulfate Extended-Release Tablets
3 DOSAGE FORMS AND STRENGTHS
4 CONTRAINDICATIONS
5 WARNINGS AND PRECAUTIONS
5.1 Addiction, Abuse, and Misuse
5.2 Life-Threatening Respiratory Depression
5.3 Neonatal Opioid Withdrawal Syndrome
5.4 Interactions with Central Nervous System Depressants
5.5 Use in Elderly, Cachectic, and Debilitated Patients
5.6 Use in Patients with Chronic Pulmonary Disease
5.7 Hypotensive Effects
5.8 Use in Patients with Head Injury or Increased Intracranial Pressure
5.9 Use in Patients with Gastrointestinal Conditions
5.10 Use in Patients with Convulsive or Seizure Disorders
5.11 Avoidance of Withdrawal
5.12 Driving and Operating Machinery
6 ADVERSE REACTIONS
6.1 Clinical Trial Experience
6.2 Post-Marketing Experience
7 DRUG INTERACTIONS
7.1 CNS Depressants
7.2 Interactions with Mixed Agonist/Antagonist and Partial Agonist Opioid Analgesics
7.3 Muscle Relaxants
7.4 Monoamine Oxidase Inhibitors (MAOIs)
7.5 Cimetidine
7.6 Diuretics
7.7 Anticholinergics
7.8 P-Glycoprotein (PGP) Inhibitors
8 USE IN SPECIFIC POPULATIONS
8.1 Pregnancy
8.2 Labor and Delivery
8.3 Nursing Mothers
8.4 Pediatric Use
8.5 Geriatric Use
9 DRUG ABUSE AND DEPENDENCE
9.1 Controlled Substance
9.2 Abuse
9.3 Dependence
10 OVERDOSAGE
11 DESCRIPTION
12 CLINICAL PHARMACOLOGY
12.1 Mechanism of Action
12.2 Pharmacodynamics
12.3 Pharmacokinetics
13 NONCLINICAL TOXICOLOGY
13.1 Carcinogenesis, Mutagenesis, Impairment of Fertility
16 HOW SUPPLIED/STORAGE AND HANDLING
17 PATIENT COUNSELING INFORMATION

*
Sections or subsections omitted from the full prescribing information are not listed.

1 INDICATIONS AND USAGE

Morphine sulfate extended-release tablets are indicated for the management of pain severe enough to require daily, around-the-clock, long-term opioid treatment and for which alternative treatment options are inadequate.

Limitations of Use

Because of the risks of addiction, abuse, and misuse with opioids, even at recommended doses, and because of the greater risks of overdose and death with extended-release opioid formulations, reserve morphine sulfate extended-release tablets for use in patients for whom alternative treatment options (e.g., non-opioid analgesics or immediate-release opioids) are ineffective, not tolerated, or would be otherwise inadequate to provide sufficient management of pain.
Morphine sulfate extended-release tablets are not indicated as an as-needed (prn) analgesic.

2 DOSAGE AND ADMINISTRATION

2.1 Initial Dosing

Morphine sulfate extended-release tablets should be prescribed only by healthcare professionals who are knowledgeable in the use of potent opioids for the management of chronic pain.

Initiate the dosing regimen for each patient individually; taking into account the patient's prior analgesic treatment experience and risk factors for addiction, abuse, and misuse [see Warnings and Precautions (5.1)]. Monitor patients closely for respiratory depression, especially within the first 24 to 72 hours of initiating therapy with morphine sulfate extended-release tablets [see WARNINGS AND PRECAUTIONS (5.2)].

Morphine sulfate extended-release tablets must be taken whole. Crushing, chewing, or dissolving morphine sulfate extended-release tablets will result in uncontrolled delivery of morphine and can lead to overdose or death [see Warnings and Precautions (5.1)].

Use of Morphine Sulfate Extended-Release Tablets as the First Opioid Analgesic

Initiate treatment with morphine sulfate extended-release tablets with 15 mg tablets orally every 8 or 12 hours.

Use of Morphine Sulfate Extended-Release Tablets in Patients who are not Opioid Tolerant

The starting dose for patients, who are not opioid-tolerant, is morphine sulfate extended-release tablets 15 mg orally every 12 hours. Patients who are opioid-tolerant are those receiving, for one week or longer, at least 60 mg oral morphine per day, 25 mcg transdermal fentanyl per hour, 30 mg oral oxycodone per day, 8 mg oral hydromorphone per day, 25 mg oral oxymorphone per day, or an equianalgesic dose of another opioid.

Use of higher starting doses in patients who are not opioid tolerant may cause fatal respiratory depression.

Conversion from Other Oral Morphine to Morphine Sulfate Extended-Release Tablets

Patients receiving other oral morphine formulations may be converted to morphine sulfate extended-release tablets by administering one-half of the patient's 24-hour requirement as morphine sulfate extended-release tablets on an every-12-hour schedule or by administering one-third of the patient's daily requirement as morphine sulfate extended-release tablets on an every-8-hour schedule.

Conversion from Other Opioids to Morphine Sulfate Extended-Release Tablets

There are no established conversion ratios for conversion from other opioids to morphine sulfate extended-release tablets defined by clinical trials. Discontinue all other around-the-clock opioid drugs when morphine sulfate extended-release tablets therapy is initiated and initiate dosing using morphine sulfate extended-release tablets 15 mg orally every 8 to 12 hours.

It is safer to underestimate a patient’s 24-hour oral morphine requirements and provide rescue medication (e.g., immediate-release morphine) than to overestimate the 24-hour oral morphine requirements and manage an adverse reaction. While useful tables of opioid equivalents are readily available, there is substantial inter-patient variability in the relative potency of different opioid drugs and products.

Conversion from Parenteral Morphine or Other Opioids (Parenteral or Oral) to Morphine Sulfate Extended-Release Tablets

When converting from parenteral morphine or other non-morphine opioids (parenteral or oral) to morphine sulfate extended-release tablets, consider the following general points:

Parenteral to oral morphine ratio: Between 2 to 6 mg of oral morphine may be required to provide analgesia equivalent to 1 mg of parenteral morphine. Typically, a dose of morphine that is approximately three times the previous daily parenteral morphine requirement is sufficient.
Other parenteral or oral non-morphine opioids to oral morphine sulfate: Specific recommendations are not available because of a lack of systematic evidence for these types of analgesic substitutions. Published relative potency data are available, but such ratios are approximations. In general, begin with half of the estimated daily morphine requirement as the initial dose, managing inadequate analgesia by supplementation with immediate-release morphine.

Conversion from Methadone to Morphine Sulfate Extended-Release Tablets

Close monitoring is of particular importance when converting methadone to other opioid agonists. The ratio between methadone and other opioid agonists may vary widely as a function of previous dose exposure. Methadone has a long half-life and can accumulate in the plasma.

2.2 Titration and Maintenance of Therapy

Individually titrate morphine sulfate extended-release tablets to a dose that provides adequate analgesia and minimizes adverse reactions. Continually reevaluate patients receiving morphine sulfate extended-release tablets to assess the maintenance of pain control and the relative incidence of adverse reactions, as well as monitoring for the development of addiction, abuse, or misuse. Frequent communication is important among the prescriber, other members of the healthcare team, the patient, and the caregiver/family during periods of changing analgesic requirements, including initial titration. During chronic therapy periodically reassess the continued need for the use of opioid analgesics.

Patients who experience breakthrough pain may require a dose increase of morphine sulfate extended-release tablets, or may need rescue medication with an appropriate dose of an immediate-release analgesic. If the level of pain increases after dose stabilization, attempt to identify the source of increased pain before increasing the morphine sulfate extended-release tablets dose. Because steady-state plasma concentrations are approximated in 1 day, morphine sulfate extended-release tablets dosage adjustments may be done every 1 to 2 days.

If unacceptable opioid-related adverse reactions are observed, the subsequent doses may be reduced. Adjust the dose to obtain an appropriate balance between management of pain and opioid-related adverse reactions.

2.3 Discontinuation of Morphine Sulfate Extended-Release Tablets

When the patient no longer requires therapy with morphine sulfate extended-release tablets, use a gradual downward titration of the dose to prevent signs and symptoms of withdrawal in the physically-dependent patient. Do not abruptly discontinue morphine sulfate extended-release tablets.

2.4 Administration of Morphine Sulfate Extended-Release Tablets

Morphine sulfate extended-release tablets must be taken whole. Crushing, chewing, or dissolving morphine sulfate extended-release tablets will result in uncontrolled delivery of morphine and can lead to overdose or death [see WARNINGS AND PRECAUTIONS (5.1)].

3 DOSAGE FORMS AND STRENGTHS

Morphine sulfate extended-release tablets 15 mg
Round, blue-colored, film-coated tablets bearing the symbol ABG on one side and 15 on the other
Morphine sulfate extended-release tablets 30 mg
Round, lavender-colored, film-coated tablets bearing the symbol ABG on one side and 30 on the other
Morphine sulfate extended-release tablets 60 mg
Round, orange-colored, film-coated tablets bearing the symbol ABG on one side and 60 on the other
Morphine sulfate extended-release tablets 100 mg*
Round, gray-colored, film-coated tablets bearing the symbol ABG on one side and 100 on the other
Morphine sulfate extended-release tablets 200 mg*
Capsule-shaped, green-colored, film-coated tablets bearing the symbol ABG on one side and 200 on the other

*100 mg and 200 mg tablets are for use in opioid-tolerant patients only

4 CONTRAINDICATIONS

Morphine sulfate extended-release tablets are contraindicated in patients with:

Significant respiratory depression
Acute or severe bronchial asthma in an unmonitored setting or in the absence of resuscitative equipment
Known or suspected paralytic ileus
Hypersensitivity (e.g., anaphylaxis) to morphine [see Adverse Reactions (6.2)]

5 WARNINGS AND PRECAUTIONS

5.1 Addiction, Abuse, and Misuse

Morphine sulfate extended-release tablets contain morphine, a Schedule II controlled substance. As an opioid, morphine sulfate extended-release tablets expose its users to the risks of addiction, abuse, and misuse. As modified-release products such as morphine sulfate extended-release tablets deliver the opioid over an extended period of time, there is a greater risk for overdose and death due to the larger amount of morphine present [see Drug Abuse and Dependence (9)].

Although the risk of addiction in any individual is unknown, it can occur in patients appropriately prescribed morphine sulfate extended-release tablets and in those who obtain the drug illicitly. Addiction can occur at recommended doses and if the drug is misused or abused.

Assess each patient’s risk for opioid addiction, abuse, or misuse prior to prescribing morphine sulfate extended-release tablets, and monitor all patients receiving opioids for development of these behaviors or conditions. Risks are increased in patients with a personal or family history of substance abuse (including drug or alcohol abuse or addiction) or mental illness (e.g., major depression). The potential for these risks should not, however, prevent the proper management of pain in any given patient. Patients at increased risk may be prescribed modified-release opioid formulations such as morphine sulfate extended-release tablets, but use in such patients necessitates intensive counseling about the risks of proper use of morphine sulfate extended-release tablets along with intensive monitoring for signs of addiction, abuse, and misuse.

Abuse or misuse of morphine sulfate extended-release tablets by crushing, chewing, snorting, or injecting the dissolved product will result in the uncontrolled delivery of morphine and can result in overdose and death [see OVERDOSAGE (10)].

Opioid agonists such as morphine sulfate extended-release tablets are sought by drug abusers and people with addiction disorders and are subject to criminal diversion. Consider these risks when prescribing or dispensing morphine sulfate extended-release tablets. Strategies to reduce these risks include prescribing the drug in the smallest appropriate quantity and advising the patient on the proper disposal of unused drug [see Patient Counseling Information (17)]. Contact local state professional licensing board or state controlled substances authority for information on how to prevent and detect abuse or diversion of this product.

5.2 Life-Threatening Respiratory Depression

Serious, life-threatening, or fatal respiratory depression has been reported with the use of modified-release opioids, even when used as recommended. Respiratory depression from opioid use, if not immediately recognized and treated, may lead to respiratory arrest and death. Management of respiratory depression may include close observation, supportive measures, and use of opioid antagonists, depending on the patient’s clinical status [see OVERDOSAGE (10)]. Carbon dioxide (CO2) retention from opioid-induced respiratory depression can exacerbate the sedating effects of opioids.

While serious, life-threatening, or fatal respiratory depression can occur at any time during the use of morphine sulfate extended-release tablets, the risk is greatest during the initiation of therapy or following a dose increase. Closely monitor patients for respiratory depression when initiating therapy with morphine sulfate extended-release tablets and following dose increases.

To reduce the risk of respiratory depression, proper dosing and titration of morphine sulfate extended-release tablets are essential [see DOSAGE AND ADMINISTRATION (2)]. Overestimating the morphine sulfate extended-release tablets dose when converting patients from another opioid product can result in a fatal overdose with the first dose.

Accidental ingestion of even one dose of morphine sulfate extended-release tablets, especially by children, can result in respiratory depression and death due to an overdose of morphine.

5.3 Neonatal Opioid Withdrawal Syndrome

Prolonged use of morphine sulfate extended-release tablets during pregnancy can result in withdrawal signs in the neonate. Neonatal opioid withdrawal syndrome, unlike opioid withdrawal syndrome in adults, may be life-threatening if not recognized and treated, and requires management according to protocols developed by neonatology experts. If opioid use is required for a prolonged period in a pregnant woman, advise the patient of the risk of neonatal opioid withdrawal syndrome and ensure that appropriate treatment will be available.

Neonatal opioid withdrawal syndrome presents as irritability, hyperactivity and abnormal sleep pattern, high pitched cry, tremor, vomiting, diarrhea and failure to gain weight. The onset, duration, and severity of neonatal opioid withdrawal syndrome vary based on the specific opioid used, duration of use, timing and amount of last maternal use, and rate of elimination of the drug by the newborn.

5.4 Interactions with Central Nervous System Depressants

Hypotension, and profound sedation, coma or respiratory depression may result if morphine sulfate extended-release tablets are used concomitantly with other central nervous system (CNS) depressants (e.g., sedatives, anxiolytics, hypnotics, neuroleptics, other opioids).

When considering the use of morphine sulfate extended-release tablets in a patient taking a CNS depressant, assess the duration of use of the CNS depressant and the patient’s response, including the degree of tolerance that has developed to CNS depression. Additionally, evaluate the patient’s use of alcohol and/or illicit drugs that cause CNS depression. If the decision to begin morphine sulfate extended-release tablets is made, start with the lowest possible dose, 15 mg every 12 hours, monitor patients for signs of sedation and respiratory depression, and consider using a lower dose of the concomitant CNS depressant [see Drug Interactions (7.1)].

5.5 Use in Elderly, Cachectic, and Debilitated Patients

Life-threatening respiratory depression is more likely to occur in elderly, cachectic, or debilitated patients as they may have altered pharmacokinetics or altered clearance compared to younger, healthier patients. Monitor such patients closely, particularly when initiating and titrating morphine sulfate extended-release tablets and when morphine sulfate extended-release tablets are given concomitantly with other drugs that depress respiration [see WARNINGS AND PRECAUTIONS (5.2)].

5.6 Use in Patients with Chronic Pulmonary Disease

Monitor patients with significant chronic obstructive pulmonary disease or cor pulmonale, and patients having a substantially decreased respiratory reserve, hypoxia, hypercapnia, or pre-existing respiratory depression for respiratory depression, particularly when initiating therapy and titrating with morphine sulfate extended-release tablets, as in these patients, even usual therapeutic doses of morphine sulfate extended-release tablets may decrease respiratory drive to the point of apnea [see WARNINGS AND PRECAUTIONS (5.2)]. Consider the use of alternative non-opioid analgesics in these patients if possible.

5.7 Hypotensive Effects

Morphine sulfate extended-release tablets may cause severe hypotension including orthostatic hypotension and syncope in ambulatory patients. There is an increased risk in patients whose ability to maintain blood pressure has already been compromised by a reduced blood volume or concurrent administration of certain CNS depressant drugs (e.g., phenothiazines or general anesthetics) [see DRUG INTERACTIONS (7.1)]. Monitor these patients for signs of hypotension after initiating or titrating the dose of morphine sulfate extended-release tablets. In patients with circulatory shock, morphine sulfate extended-release tablets may cause vasodilation that can further reduce cardiac output and blood pressure. Avoid the use of morphine sulfate extended-release tablets in patients with circulatory shock.

5.8 Use in Patients with Head Injury or Increased Intracranial Pressure

Monitor patients taking morphine sulfate extended-release tablets who may be susceptible to the intracranial effects of CO2 retention (e.g., those with evidence of increased intracranial pressure or brain tumors) for signs of sedation and respiratory depression, particularly when initiating therapy with morphine sulfate extended-release tablets. Morphine sulfate extended-release tablets may reduce respiratory drive, and the resultant CO2 retention can further increase intracranial pressure. Opioids may also obscure the clinical course in a patient with a head injury.

Avoid the use of morphine sulfate extended-release tablets in patients with impaired consciousness or coma.

5.9 Use in Patients with Gastrointestinal Conditions

Morphine sulfate extended-release tablets are contraindicated in patients with paralytic ileus. Avoid the use of morphine sulfate extended-release tablets in patients with other GI obstruction.

The morphine in morphine sulfate extended-release tablets may cause spasm of the sphincter of Oddi. Monitor patients with biliary tract disease, including acute pancreatitis, for worsening symptoms. Opioids may cause increases in the serum amylase.

5.10 Use in Patients with Convulsive or Seizure Disorders

The morphine in morphine sulfate extended-release tablets may aggravate convulsions in patients with convulsive disorders, and may induce or aggravate seizures in some clinical settings. Monitor patients with a history of seizure disorders for worsened seizure control during morphine sulfate extended-release tablet therapy.

5.11 Avoidance of Withdrawal

Avoid the use of mixed agonist/antagonist (i.e., pentazocine, nalbuphine, and butorphanol) or partial agonist (buprenorphine) analgesics in patients who have received or are receiving a course of therapy with a full opioid agonist analgesic, morphine sulfate extended-release tablets. In these patients, mixed agonists/antagonist and partial agonist analgesics may reduce the analgesic effect and/or may precipitate withdrawal symptoms.

When discontinuing morphine sulfate extended-release tablets, gradually taper the dose [see DOSAGE AND ADMINISTRATION (2.3)]. Do not abruptly discontinue morphine sulfate extended-release tablets.

5.12 Driving and Operating Machinery

Morphine sulfate extended-release tablets may impair the mental or physical abilities needed to perform potentially hazardous activities such as driving a car or operating machinery. Warn patients not to drive or operate dangerous machinery unless they are tolerant to the effects of morphine sulfate extended-release tablets and know how they will react to the medication.

6 ADVERSE REACTIONS

The following serious adverse reactions are described elsewhere in the labeling:

Addiction, Abuse, and Misuse [see Warnings and Precautions (5.1)]
Life-Threatening Respiratory Depression [see WARNINGS AND PRECAUTIONS (5.2)]
Neonatal Opioid Withdrawal Syndrome [see Warnings and Precautions (5.3)]
Interactions with Other CNS Depressants [see WARNINGS AND PRECAUTIONS (5.4)]
Hypotensive Effect [see WARNINGS AND PRECAUTIONS (5.7)]
Gastrointestinal Effects [see WARNINGS AND PRECAUTIONS (5.9)]
Seizures [see WARNINGS AND PRECAUTIONS (5.10)]

6.1 Clinical Trial Experience

Because clinical trials are conducted under widely varying conditions, adverse reaction rates observed in the clinical trials of a drug cannot be directly compared to rates in the clinical trials of another drug and may not reflect the rates observed in practice.

Morphine sulfate extended-release tablets may increase the risk of serious adverse reactions such as those observed with other opioid analgesics, including respiratory depression, apnea, respiratory arrest, circulatory depression, hypotension, or shock [see OVERDOSAGE (10)].

Most Frequently Observed Reactions

In clinical trials, the most common adverse reactions with morphine sulfate extended-release tablets were constipation, dizziness, sedation, nausea, vomiting, sweating, dysphoria, and euphoric mood.

Some of these effects seem to be more prominent in ambulatory patients and in those not experiencing severe pain.

Less Frequently Observed Reactions

Cardiovascular disorders: tachycardia, bradycardia, palpitations

Eye disorders: visual impairment, vision blurred, diplopia, miosis

Gastrointestinal disorders: dry mouth, diarrhea, abdominal pain, constipation, dyspepsia

General disorders and administration site conditions: chills, feeling abnormal, edema, edema peripheral, weakness

Hepatobiliary disorders: biliary colic

Metabolism and nutrition disorders: anorexia

Musculoskeletal and connective tissue disorders: muscle rigidity, muscle twitching

Nervous system disorders: presyncope, syncope, headache, tremor, uncoordinated muscle movements, convulsion, intracranial pressure increased, taste alteration, paresthesia, nystagmus

Psychiatric disorders: agitation, mood altered, anxiety, depression, abnormal dreams, hallucination, disorientation, insomnia

Renal and urinary disorders: urinary retention, urinary hesitation, antidiuretic effects

Reproductive system and breast disorders: reduced libido and/or potency

Respiratory, thoracic and mediastinal disorders: laryngospasm

Skin and subcutaneous tissue disorders: pruritus, urticaria, rash

Vascular disorders: flushing, hypotension, hypertension

6.2 Post-Marketing Experience

The following adverse reactions have been identified during postapproval use of morphine sulfate extended-release tablets: amenorrhea, asthenia, bronchospasm, confusional state, drug hypersensitivity, fatigue, hyperalgesia, hypertonia, ileus, increased hepatic enzymes, intestinal obstruction, lethargy, malaise, pulmonary edema, thinking disturbances, somnolence, and vertigo.

Anaphylaxis has been reported with ingredients contained in morphine sulfate extended-release tablets. Advise patients how to recognize such a reaction and when to seek medical attention.

7 DRUG INTERACTIONS

7.1 CNS Depressants

The concomitant use of morphine sulfate extended-release tablets with other CNS depressants including sedatives, hypnotics, tranquilizers, general anesthetics, phenothiazines, other opioids, and alcohol can increase the risk of respiratory depression, profound sedation, coma, and death. Monitor patients receiving CNS depressants and morphine sulfate extended-release tablets for signs of respiratory depression, sedation, and hypotension.

When combined therapy with any of the above medications is considered, the dose of one or both agents should be reduced [see Dosage and Administration (2.2) and Warnings and Precautions (5.4)].

7.2 Interactions with Mixed Agonist/Antagonist and Partial Agonist Opioid Analgesics

Mixed agonist/antagonist (i.e., pentazocine, nalbuphine, and butorphanol) and partial agonist (buprenorphine) analgesics may reduce the analgesic effect of morphine sulfate extended-release tablets or precipitate withdrawal symptoms. Avoid the use of agonist/antagonist and partial agonist analgesics in patients receiving morphine sulfate extended-release tablets.

7.3 Muscle Relaxants

Morphine may enhance the neuromuscular blocking action of skeletal muscle relaxants and produce an increased degree of respiratory depression. Monitor patients receiving muscle relaxants and morphine sulfate extended-release tablets for signs of respiratory depression that may be greater than otherwise expected.

7.4 Monoamine Oxidase Inhibitors (MAOIs)

The effects of morphine may be potentiated by MAOIs. Monitor patients on concurrent therapy with an MAOI and morphine sulfate extended-release tablets for increased respiratory and central nervous system depression. MAOIs have been reported to potentiate the effects of morphine anxiety, confusion, and significant depression of respiration or coma. Morphine sulfate extended-release tablets should not be used in patients taking MAOIs or within 14 days of stopping such treatment.

7.5 Cimetidine

Cimetidine can potentiate morphine-induced respiratory depression. There is a report of confusion and severe respiratory depression when a patient undergoing hemodialysis was concurrently administered morphine and cimetidine. Monitor patients for respiratory depression when morphine sulfate extended-release tablets and cimetidine are used concurrently.

7.6 Diuretics

Morphine can reduce the efficacy of diuretics by inducing the release of antidiuretic hormone. Morphine may also lead to acute retention of urine by causing spasm of the sphincter of the bladder, particularly in men with enlarged prostates.

7.7 Anticholinergics

Anticholinergics or other medications with anticholinergic activity when used concurrently with opioid analgesics may result in increased risk of urinary retention and/or severe constipation, which may lead to paralytic ileus. Monitor patients for signs of urinary retention or reduced gastric motility when morphine sulfate extended-release tablets are used concurrently with anticholinergic drugs.

7.8 P-Glycoprotein (PGP) Inhibitors

PGP-inhibitors (e.g., quinidine) may increase the absorption/exposure of morphine sulfate by about two-fold. Therefore, monitor patients for signs of respiratory and central nervous system depression when morphine sulfate extended-release tablets are used concurrently with PGP inhibitors.

8 USE IN SPECIFIC POPULATIONS

8.1 Pregnancy

Clinical Considerations

Fetal/neonatal adverse reactions

Prolonged use of opioid analgesics during pregnancy for medical or nonmedical purposes can result in physical dependence in the neonate and neonatal opioid withdrawal syndrome shortly after birth. Observe newborns for symptoms of neonatal opioid withdrawal syndrome, such as poor feeding, diarrhea, irritability, tremor, rigidity, and seizures, and manage accordingly [see Warnings and Precautions (5.3)].

Teratogenic Effects -Pregnancy Category C

There are no adequate and well-controlled studies in pregnant women. Morphine sulfate extended-release tablets should be used during pregnancy only if the potential benefit justifies the potential risk to the fetus.

In humans, the frequency of congenital anomalies has been reported to be no greater than expected among the children of 70 women who were treated with morphine during the first four months of pregnancy or in 448 women treated with morphine anytime during pregnancy. Furthermore, no malformations were observed in the infant of a woman who attempted suicide by taking an overdose of morphine and other medication during the first trimester of pregnancy.

Several literature reports indicate that morphine administered subcutaneously during the early gestational period in mice and hamsters produced neurological, soft tissue and skeletal abnormalities. With one exception, the effects that have been reported were following doses that were maternally toxic and the abnormalities noted were characteristic of those observed when maternal toxicity is present. In one study, following subcutaneous infusion of doses greater than or equal to 0.15 mg/kg to mice, exencephaly, hydronephrosis, intestinal hemorrhage, split supraoccipital, malformed sternebrae, and malformed xiphoid were noted in the absence of maternal toxicity. In the hamster, morphine sulfate given subcutaneously on gestation day 8 produced exencephaly and cranioschisis. In rats treated with subcutaneous infusions of morphine during the period of organogenesis, no teratogenicity was observed. No maternal toxicity was observed in this study; however, increased mortality and growth retardation were seen in the offspring. In two studies performed in the rabbit, no evidence of teratogenicity was reported at subcutaneous doses up to 100 mg/kg.

Non-Teratogenic Effects

Infants born to mothers who have taken opioids chronically may exhibit neonatal withdrawal syndrome [see Warnings and Precautions (5.3)], reversible reduction in brain volume, small size, decreased ventilatory response to CO2 and increased risk of sudden infant death syndrome. Morphine sulfate should be used by a pregnant woman only if the need for opioid analgesia clearly outweighs the potential risks to the fetus.

Controlled studies of chronic in utero morphine exposure in pregnant women have not been conducted. Published literature has reported that exposure to morphine during pregnancy in animals is associated with reduction in growth and a host of behavioral abnormalities in the offspring. Morphine treatment during gestational periods of organogenesis in rats, hamsters, guinea pigs and rabbits resulted in the following treatment-related embryotoxicity and neonatal toxicity in one or more studies: decreased litter size, embryo-fetal viability, fetal and neonatal body weights, absolute brain and cerebellar weights, delayed motor and sexual maturation, and increased neonatal mortality, cyanosis and hypothermia. Decreased fertility in female offspring, and decreased plasma and testicular levels of luteinizing hormone and testosterone, decreased testes weights, seminiferous tubule shrinkage, germinal cell aplasia, and decreased spermatogenesis in male offspring were also observed. Decreased litter size and viability were observed in the offspring of male rats administered morphine (25 mg/kg, IP) for 1 day prior to mating. Behavioral abnormalities resulting from chronic morphine exposure of fetal animals included altered reflex and motor skill development, mild withdrawal, and altered responsiveness to morphine persisting into adulthood.

8.2 Labor and Delivery

Opioids cross the placenta and may produce respiratory depression in neonates. Morphine sulfate extended-release tablets are not for use in women during and immediately prior to labor, when shorter acting analgesics or other analgesic techniques are more appropriate. Opioid analgesics can prolong labor through actions that temporarily reduce the strength, duration, and frequency of uterine contractions. However, this effect is not consistent and may be offset by an increased rate of cervical dilatation, which tends to shorten labor.

8.3 Nursing Mothers

Morphine is excreted in breast milk, with a milk to plasma morphine AUC ratio of approximately 2.5:1. The amount of morphine received by the infant varies depending on the maternal plasma concentration, the amount of milk ingested by the infant, and the extent of first pass metabolism.

Withdrawal signs can occur in breast-feeding infants when maternal administration of morphine is stopped.

Because of the potential for adverse reactions in nursing infants from morphine sulfate extended-release tablets, a decision should be made whether to discontinue nursing or discontinue the drug, taking into account the importance of the drug to the mother.

8.4 Pediatric Use

The safety and effectiveness in pediatric patients below the age of 18 have not been established.

8.5 Geriatric Use

The pharmacokinetics of morphine sulfate extended-release tablets has not been studied in elderly patients. Clinical studies of morphine sulfate extended-release tablets did not include sufficient numbers of subjects aged 65 and over to determine whether they respond differently from younger subjects. In general, dose selection for an elderly patient should be cautious, usually starting at the low end of the dosing range, reflecting the greater frequency of decreased hepatic, renal, or cardiac function, and of concomitant disease or other drug therapy.

9 DRUG ABUSE AND DEPENDENCE

9.1 Controlled Substance

Morphine sulfate extended-release tablets contain morphine, a Schedule II controlled substance with a high potential for abuse similar to other opioids including fentanyl, hydromorphone, methadone, oxycodone, and oxymorphone. Morphine sulfate extended-release tablets can be abused and is subject to misuse, addiction, and criminal diversion [see WARNINGS AND PRECAUTIONS (5.1)].

The high drug content in extended-release formulations adds to the risk of adverse outcomes from abuse and misuse.

9.2 Abuse

All patients treated with opioids require careful monitoring for signs of abuse and addiction, since use of opioid analgesic products carries the risk of addiction even under appropriate medical use. Drug abuse is the intentional non-therapeutic use of an over-the-counter or prescription drug, even once, for its rewarding psychological or physiological effects. Drug abuse includes, but is not limited to the following examples: the use of a prescription or over-the-counter drug to get “high”, or the use of steroids for performance enhancement and muscle build up.

Drug addiction is a cluster of behavioral, cognitive, and physiological phenomena that develop after repeated substance use and include: a strong desire to take the drug, difficulties in controlling its use, persisting in its use despite harmful consequences, a higher priority given to drug use than to other activities and obligations, increased tolerance, and sometimes a physical withdrawal.

"Drug seeking" behavior is very common to addicts and drug abusers. Drug-seeking tactics include emergency calls or visits near the end of office hours, refusal to undergo appropriate examination, testing or referral, repeated claims of loss of prescriptions, tampering with prescriptions and reluctance to provide prior medical records or contact information for other treating physician(s). “Doctor shopping” (visiting multiple prescribers) to obtain additional prescriptions is common among drug abusers and people suffering from untreated addiction.

Preoccupation with achieving adequate pain relief can be appropriate behavior in a patient with poor pain control.

Abuse and addiction are separate and distinct from physical dependence and tolerance. Physicians should be aware that addiction may not be accompanied by concurrent tolerance and symptoms of physical dependence in all addicts. In addition, abuse of opioids can occur in the absence of true addiction.

Morphine sulfate extended-release tablets, like other opioids, can be diverted for non-medical use into illicit channels of distribution. Careful recordkeeping of prescribing information, including quantity, frequency, and renewal requests as required by state law, is strongly advised.
Proper assessment of the patient, proper prescribing practices, periodic reevaluation of therapy, and proper dispensing and storage are appropriate measures that help to reduce abuse of opioid drugs.

Risks Specific to Abuse of Morphine Sulfate Extended-Release Tablets

Morphine sulfate extended-release tablets are for oral use only. Abuse of morphine sulfate extended-release tablets poses a risk of overdose and death. This risk is increased with concurrent abuse of morphine sulfate extended-release tablets with alcohol and other substances. Taking cut, broken, chewed, crushed, or dissolved morphine sulfate extended-release tablets enhances drug release and increases the risk of overdose and death.

Due to the presence of talc as one of the excipients in morphine sulfate extended-release tablets, parenteral abuse can be expected to result in local tissue necrosis, infection, pulmonary granulomas, and increased risk of endocarditis and valvular heart injury. Parenteral drug abuse is commonly associated with transmission of infectious diseases such as hepatitis and HIV.

9.3 Dependence

Both tolerance and physical dependence can develop during chronic opioid therapy. Tolerance is the need for increasing doses of opioids to maintain a defined effect such as analgesia (in the absence of disease progression or other external factors). Tolerance may occur to both the desired and undesired effects of drugs, and may develop at different rates for different effects.

Physical dependence results in withdrawal symptoms after abrupt discontinuation or a significant dose reduction of a drug. Withdrawal also may be precipitated through the administration of drugs with opioid antagonist activity, e.g., naloxone, nalmefene, mixed agonist/antagonist analgesics (pentazocine, butorphanol, nalbuphine), or partial agonists (buprenorphine). Physical dependence may not occur to a clinically significant degree until after several days to weeks of continued opioid usage.

Morphine sulfate extended-release tablets should not be abruptly discontinued [see DOSAGE AND ADMINISTRATION (2.3)]. If morphine sulfate extended-release tablets are abruptly discontinued in a physically-dependent patient, an abstinence syndrome may occur. Some or all of the following can characterize this syndrome: restlessness, lacrimation, rhinorrhea, yawning, perspiration, chills, myalgia, and mydriasis. Other signs and symptoms also may develop, including: irritability, anxiety, backache, joint pain, weakness, abdominal cramps, insomnia, nausea, anorexia, vomiting, diarrhea, or increased blood pressure, respiratory rate, or heart rate.

Infants born to mothers physically dependent on opioids will also be physically dependent and may exhibit respiratory difficulties and withdrawal signs [see Use in Specific Populations (8.1)].

10 OVERDOSAGE

Clinical Presentation

Acute overdosage with morphine is manifested by respiratory depression, somnolence progressing to stupor or coma, skeletal muscle flaccidity, cold and clammy skin, constricted pupils, and, in some cases, pulmonary edema, bradycardia, hypotension, and death. Marked mydriasis rather than miosis may be seen due to severe hypoxia in overdose situations.

Treatment of Overdose

In case of overdose, priorities are the reestablishment of a patent and protected airway and institution of assisted or controlled ventilation if needed. Employ other supportive measures (including oxygen, vasopressors) in the management of circulatory shock and pulmonary edema as indicated. Cardiac arrest or arrhythmias will require advanced life support techniques.

The opioid antagonists, naloxone or nalmefene, are specific antidotes to respiratory depression resulting from opioid overdose. Opioid antagonists should not be administered in the absence of clinically significant respiratory or circulatory depression secondary to morphine overdose. Such agents should be administered cautiously to persons who are known, or suspected to be physically dependent on morphine sulfate extended-release tablets. In such cases, an abrupt or complete reversal of opioid effects may precipitate an acute withdrawal syndrome.

Because the duration of reversal would be expected to be less than the duration of action of morphine in morphine sulfate extended-release tablets, carefully monitor the patient until spontaneous respiration is reliably reestablished. Morphine sulfate extended-release tablets will continue to release morphine and add to the morphine load for 24 to 48 hours or longer following ingestion necessitating prolonged monitoring. If the response to opioid antagonists is suboptimal or not sustained, additional antagonist should be administered as directed in the product’s prescribing information.

In an individual physically dependent on opioids, administration of the usual dose of the antagonist will precipitate an acute withdrawal syndrome. The severity of the withdrawal symptoms experienced will depend on the degree of physical dependence and the dose of the antagonist administered. If a decision is made to treat serious respiratory depression in the physically dependent patient, administration of the antagonist should be begun with care and by titration with smaller than usual doses of the antagonist.

11 DESCRIPTION

Morphine Sulfate Extended-Release Tablets are for oral use and contain morphine sulfate, an agonist at the mu-opioid receptor.

Each tablet contains the following inactive ingredients common to all strengths: cetostearyl alcohol, hydroxyethyl cellulose, hypromellose, magnesium stearate, polyethylene glycol, talc, and titanium dioxide.

The tablet strengths describe the amount of morphine per tablet as the pentahydrated sulfate salt (morphine sulfate).

The 15 mg tablets also contain: FD&C Blue No. 2, lactose monohydrate, polysorbate 80

The 30 mg tablets also contain: D&C Red No. 7, FD&C Blue No. 1, lactose monohydrate, polysorbate 80

The 60 mg tablets also contain: D&C Red No. 30, D&C Yellow No. 10, hydroxypropyl cellulose, lactose monohydrate

The 100 mg tablets also contain: black iron oxide

The 200 mg tablets also contain: D&C Yellow No. 10, FD&C Blue No. 1, hydroxypropyl cellulose

Morphine sulfate is an odorless, white, crystalline powder with a bitter taste. It has a solubility of 1 in 21 parts of water and 1 in 1000 parts of alcohol, but is practically insoluble in chloroform or ether. The octanol: water partition coefficient of morphine is 1.42 at physiologic pH and the pKb is 7.9 for the tertiary nitrogen (mostly ionized at pH 7.4). Its structural formula is:

12 CLINICAL PHARMACOLOGY

12.1 Mechanism of Action

Morphine sulfate, an opioid agonist, is relatively selective for the mu receptor, although it can interact with other opioid receptors at higher doses. In addition to analgesia, the widely diverse effects of morphine sulfate include analgesia, dysphoria, euphoria, somnolence, respiratory depression, diminished gastrointestinal motility, altered circulatory dynamics, histamine release, physical dependence, and alterations of the endocrine and autonomic nervous systems.

Morphine produces both its therapeutic and its adverse effects by interaction with one or more classes of specific opioid receptors located throughout the body. Morphine acts as a full agonist, binding with and activating opioid receptors at sites in the peri-aqueductal and peri-ventricular grey matter, the ventro-medial medulla and the spinal cord to produce analgesia.

12.2 Pharmacodynamics

Plasma Level-Analgesia Relationships

While plasma morphine-efficacy relationships can be demonstrated in non-tolerant individuals, they are influenced by a wide variety of factors and are not generally useful as a guide to the clinical use of morphine. Dosages of morphine should be chosen and must be titrated on the basis of clinical evaluation of the patient and the balance between therapeutic and adverse effects.

CNS Depressant/Alcohol Interaction

Additive pharmacodynamic effects may be expected when morphine sulfate extended-release tablets are used in conjunction with alcohol, other opioids, or illicit drugs that cause central nervous system depression.

Effects on the Central Nervous System

The principal actions of therapeutic value of morphine are analgesia and sedation. Specific CNS opiate receptors for endogenous compounds with opioid-like activity have been identified throughout the brain and spinal cord and are likely to play a role in the expression of analgesic effects.

Morphine produces respiratory depression by direct action on brainstem respiratory centers. The mechanism of respiratory depression involves a reduction in the responsiveness of the brainstem respiratory centers to increases in carbon dioxide tension, and to electrical stimulation.

Morphine depresses the cough reflex by direct effect on the cough center in the medulla. Morphine causes miosis, even in total darkness. Pinpoint pupils are a sign of narcotic overdose but are not pathognomonic (e.g., pontine lesions of hemorrhagic or ischemic origins may produce similar findings). Marked mydriasis rather than miosis may be seen with worsening hypoxia.

Effects on the Gastrointestinal Tract and Other Smooth Muscle

Morphine causes a reduction in motility associated with an increase in smooth muscle tone in the antrum of the stomach and in the duodenum. Digestion of food is delayed in the small intestine and propulsive contractions are decreased. Propulsive peristaltic waves in the colon are decreased, while tone may be increased to the point of spasm. The end result is constipation. Morphine can cause a marked reduction in gastric, biliary and pancreatic secretions, spasm of the sphincter of Oddi, and transient elevations in serum amylase.

Effects on the Cardiovascular System

Morphine produces peripheral vasodilation which may result in orthostatic hypotension. Release of histamine can occur and may contribute to opioid-induced hypotension. Manifestations of histamine release and/or peripheral vasodilation may include pruritus, flushing, red eyes, and sweating.

Effects on the Endocrine System

Opioids inhibit the secretion of ACTH, cortisol, testosterone, and luteinizing hormone (LH) in humans. They also stimulate prolactin, growth hormone (GH) secretion, and pancreatic secretion of insulin and glucagon.

Effects on the Immune System

Opioids have been shown to have a variety of effects on components of the immune system in in vitroand animal models. The clinical significance of these findings is unknown. Overall, the effects of opioids appear to be modestly immunosuppressive.

12.3 Pharmacokinetics

Morphine sulfate extended-release tablets are an extended-release tablet containing morphine sulfate. Morphine is released from morphine sulfate extended-release tablets somewhat more slowly than from immediate-release oral preparations. Following oral administration of a given dose of morphine, the amount ultimately absorbed is essentially the same whether the source is morphine sulfate extended-release tablets or an immediate-release formulation. Because of pre-systemic elimination (i.e., metabolism in the gut wall and liver) only about 40% of the administered dose reaches the central compartment.

Absorption

The oral bioavailability of morphine is approximately 20 to 40%. When morphine sulfate extended-release tablets are given on a fixed dosing regimen, steady-state is achieved in about a day.

Food Effect

The effect of food upon the systemic bioavailability of morphine sulfate extended-release tablets has not been systematically evaluated for all strengths. One study, conducted with the 30 mg morphine sulfate extended-release tablets, showed no significant differences in Cmax and AUC (0-24h) values, whether the tablet was taken while fasting or with a high-fat breakfast.

Distribution

Once absorbed, morphine is distributed to skeletal muscle, kidneys, liver, intestinal tract, lungs, spleen, and brain. Morphine also crosses placental membranes and has been found in breast milk. The volume of distribution (Vd) for morphine is approximately 3 to 4 liters per kilogram and morphine is 30 to 35% reversibly bound to plasma proteins.

Metabolism

The major pathways of morphine metabolism include glucuronidation to produce metabolites including morphine-3-glucuronide, M3G (about 50%) and morphine-6-glucuronide, M6G (about 5 to 15%) and sulfation in the liver to produce morphine-3-etheral sulfate. A small fraction (less than 5%) of morphine is demethylated. M6G has been shown to have analgesic activity but crosses the blood-brain barrier poorly, while M3G has no significant analgesic activity.

Excretion

The elimination of morphine occurs primarily as renal excretion of M3G and its effective half-life after intravenous administration is normally 2 to 4 hours. Approximately 10% of the dose is excreted unchanged in urine. In some studies involving longer periods of plasma sampling, a longer terminal half-life of about 15 hours was reported. A small amount of the glucuronide conjugate is excreted in the bile, and there is some minor enterohepatic recycling.

Specific Populations

Geriatric Patients

The pharmacokinetics of morphine sulfate extended-release tablets have not been studied in elderly patients.

Pediatric Patients

The pharmacokinetics of morphine sulfate extended-release tablets have not been studied in pediatric patients below the age of 18.

Gender

A gender analysis of pharmacokinetic data from healthy subjects taking morphine sulfate extended-release tablets indicated that morphine concentrations were similar in males and females.

Race

Chinese subjects given intravenous morphine had a higher clearance when compared to Caucasian subjects (1852 +/- 116 ml/min compared to 1495 +/- 80 ml/min).

Hepatic Impairment

Morphine pharmacokinetics are altered in individuals with cirrhosis. Clearance was found to decrease with a corresponding increase in half-life. The M3G and M6G to morphine plasma AUC ratios also decreased in these subjects, indicating diminished metabolic activity. Adequate studies of the pharmacokinetics of morphine in patients with severe hepatic impairment have not been conducted.

Renal Impairment

Morphine pharmacokinetics are altered in patients with renal failure. The AUC is increased and clearance is decreased and the metabolites, M3G and M6G, may accumulate to much higher plasma levels in patients with renal failure as compared to patients with normal renal function. Adequate studies of the pharmacokinetics of morphine in patients with severe renal impairment have not been conducted.

13 NONCLINICAL TOXICOLOGY

13.1 Carcinogenesis, Mutagenesis, Impairment of Fertility

Carcinogenesis: Studies in animals to evaluate the carcinogenic potential of morphine have not been conducted.

Mutagenesis: No formal studies to assess the mutagenic potential of morphine have been conducted. In the published literature, morphine was found to be mutagenic in vitro increasing DNA fragmentation in human T-cells. Morphine was reported to be mutagenic in the in vivo mouse micronucleus assay and positive for the induction of chromosomal aberrations in mouse spermatids and murine lymphocytes. Mechanistic studies suggest that the in vivo clastogenic effects reported with morphine in mice may be related to increases in glucocorticoid levels produced by morphine in this species. In contrast to the above positive findings, in vitro studies in the literature have also shown that morphine did not induce chromosomal aberrations in human leukocytes or translocations or lethal mutations in Drosophila.

Impairment of Fertility: No formal nonclinical studies to assess the potential of morphine to impair fertility have been conducted. Several nonclinical studies from the literature have demonstrated adverse effects on male fertility in the rat from exposure to morphine. One study in which male rats were administered morphine sulfate subcutaneously prior to mating (up to 30 mg/kg twice daily) and during mating (20 mg/kg twice daily) with untreated females, a number of adverse reproductive effects including reduction in total pregnancies, higher incidence of pseudopregnancies, and reduction in implantation sites were seen. Studies from the literature have also reported changes in hormonal levels (i.e., testosterone, luteinizing hormone, serum corticosterone) following treatment with morphine. These changes may be associated with the reported effects on fertility in the rat.

16 HOW SUPPLIED/STORAGE AND HANDLING

Morphine Sulfate Extended-Release Tablets are available as follows:

15 mg - round, blue-colored, film-coated tablet bearing the symbol ABG on one side and 15 on the other.

Bottles (opaque plastic) of 100..........................................................................NDC 42858-801-01

30 mg - round, lavender-colored, film-coated tablet bearing the symbol ABG on one side and 30 on the other.

Bottles (opaque plastic) of 100..........................................................................NDC 42858-802-01

60 mg - round, orange-colored, film-coated tablet bearing the symbol ABG on one side and 60 on the other.

Bottles (opaque plastic) of 100..........................................................................NDC 42858-803-01

100 mg - round, gray-colored, film-coated tablet bearing the symbol ABG on one side and 100 on the other.

Bottles (opaque plastic) of 100..........................................................................NDC 42858-804-01

200 mg - capsule-shaped, green-colored, film-coated tablet bearing the symbol ABG on one side and 200 on the other.

Bottles (opaque plastic) of 100..........................................................................NDC 42858-805-01

Store at 25°C (77°F); excursions permitted between 15° to 30°C (59° to 86°F). [See USP Controlled Room Temperature].

Dispense in a tight, light-resistant container.

CAUTION

DEA FORM REQUIRED

17 PATIENT COUNSELING INFORMATION

Advise the patient to read the FDA-approved patient labeling (Medication Guide).

Addiction, Abuse, and Misuse

Inform patients that the use of morphine sulfate extended-release tablets, even when taken as recommended, can result in addiction, abuse, and misuse, which can lead to overdose or death [see Warnings and Precautions (5.1)]. Instruct patients not to share morphine sulfate extended-release tablets with others and to take steps to protect morphine sulfate extended-release tablets from theft or misuse.

Life-Threatening Respiratory Depression

Inform patients of the risk of life-threatening respiratory depression, including information that the risk is greatest when starting morphine sulfate extended-release tablets or when the dose is increased, and that it can occur even at recommended doses [see Warnings and Precautions (5.2)]. Advise patients how to recognize respiratory depression and to seek medical attention if breathing difficulties develop.

Accidental Ingestion

Inform patients that accidental ingestion, especially in children, may result in respiratory depression or death [see Warnings and Precautions (5.2)]. Instruct patients to take steps to store morphine sulfate extended-release tablets securely and to dispose of unused morphine sulfate extended-release tablets by flushing the tablets down the toilet.

Neonatal Opioid Withdrawal Syndrome

Inform female patients of reproductive potential that prolonged use of morphine sulfate extended-release tablets during pregnancy can result in neonatal opioid withdrawal syndrome, which may be life-threatening if not recognized and treated [see Warnings and Precautions (5.3)].

Interactions with Alcohol and other CNS Depressants

Inform patients that potentially serious additive effects may occur if morphine sulfate extended-release tablets are used with alcohol or other CNS depressants, and not to use such drugs unless supervised by a health care provider.

Important Administration Instructions

Instruct patients how to properly take morphine sulfate extended-release tablets, including the following:

Swallowing morphine sulfate extended-release tablets whole
Not crushing, chewing, or dissolving the tablets
Using morphine sulfate extended-release tablets exactly as prescribed to reduce the risk of life-threatening adverse reactions (e.g., respiratory depression)
Not discontinuing morphine sulfate extended-release tablets without first discussing the need for a tapering regimen with the prescriber

Hypotension

Inform patients that morphine sulfate extended-release tablets may cause orthostatic hypotension and syncope. Instruct patients how to recognize symptoms of low blood pressure and how to reduce the risk of serious consequences should hypotension occur (e.g., sit or lie down, carefully rise from a sitting or lying position).

Driving or Operating Heavy Machinery

Inform patients that morphine sulfate extended-release tablets may impair the ability to perform potentially hazardous activities such as driving a car or operating heavy machinery. Advise patients not to perform such tasks until they know how they will react to the medication.

Constipation

Advise patients of the potential for severe constipation, including management instructions and when to seek medical attention.

Anaphylaxis

Inform patients that anaphylaxis has been reported with ingredients contained in morphine sulfate extended-release tablets. Advise patients how to recognize such a reaction and when to seek medical attention.

Pregnancy

Advise female patients that morphine sulfate extended-release tablets can cause fetal harm and to inform the prescriber if they are pregnant or plan to become pregnant.

Healthcare professionals can telephone Rhodes Pharmaceuticals L.P. (1-888-827-0616) for information on this product.

Disposal of Unused Morphine Sulfate Extended-Release Tablets

Advise patients to flush the unused tablets down the toilet when morphine sulfate extended-release tablets are no longer needed.

Marketed by:
Rhodes Pharmaceuticals L.P.
Coventry, RI 02816
302942-0C

Revised 10/2016

MEDICATION GUIDE

Morphine Sulfate (Mor-feen-SUL-fate) Extended-Release (ER) Tablets, CII

Morphine sulfate ER tablets are:

A strong prescription pain medicine that contains an opioid (narcotic) that is used to manage pain severe enough to require daily around-the-clock, long-term treatment with an opioid, when other pain treatments such as non-opioid pain medicines or immediate-release opioid medicines do not treat your pain well enough or you cannot tolerate them.
A long-acting (extended-release) opioid pain medicine that can put you at risk for overdose and death. Even if you take your dose correctly as prescribed you are at risk for opioid addiction, abuse, and misuse that can lead to death.
Not for use to treat pain that is not around-the-clock.

Important information about morphine sulfate ER tablets:

Get emergency help right away if you take too much morphine sulfate ER tablets (overdose). When you first start taking morphine sulfate ER tablets, when your dose is changed, or if you take too much (overdose), serious or life-threatening breathing problems that can lead to death may occur.
Never give anyone else your morphine sulfate ER tablets. They could die from taking it. Store morphine sulfate ER tablets away from children and in a safe place to prevent stealing or abuse. Selling or giving away morphine sulfate ER tablets is against the law.

Do not take morphine sulfate ER tablets if you have:

severe asthma, trouble breathing, or other lung problems.
a bowel blockage or have narrowing of the stomach or intestines.

Before taking morphine sulfate ER tablets, tell your healthcare provider if you have a history of:

head injury, seizures
liver, kidney, thyroid problems
problems urinating
pancreas or gallbladder problems
abuse of street or prescription drugs, alcohol addiction, or mental health problems.

Tell your healthcare provider if you are:

pregnant or planning to become pregnant. Prolonged use of morphine sulfate ER tablets during pregnancy can cause withdrawal symptoms in your newborn baby that could be life-threatening if not recognized and treated.
breastfeeding. Morphine sulfate ER tablets pass into breast milk and may harm your baby.
taking prescription or over-the-counter medicines, vitamins, or herbal supplements. Taking morphine sulfate ER tablets with certain other medicines can cause serious side effects.

When taking morphine sulfate ER tablets:

Do not change your dose. Take morphine sulfate ER tablets exactly as prescribed by your healthcare provider.
Take your prescribed dose every 8 to 12 hours, as directed by your healthcare provider. Do not take more than your prescribed dose. If you miss a dose, take your next dose at the usual time.
Swallow morphine sulfate ER tablets whole. Do not cut, break, chew, crush, dissolve, snort, or inject morphine sulfate ER tablets because this may cause you to overdose and die.
Call your healthcare provider if the dose you are taking does not control your pain.
Do not stop taking morphine sulfate ER tablets without talking to your healthcare provider.
After you stop taking morphine sulfate ER tablets, flush any unused tablets down the toilet.

While taking morphine sulfate ER tablets DO NOT:

Drive or operate heavy machinery, until you know how morphine sulfate ER tablets affect you. Morphine sulfate ER tablets can make you sleepy, dizzy, or lightheaded.
Drink alcohol or use prescription or over-the-counter medicines that contain alcohol. Using products containing alcohol during treatment with morphine sulfate ER tablets may cause you to overdose and die.

The possible side effects of morphine sulfate ER tablets are:

constipation, nausea, sleepiness, vomiting, tiredness, headache, dizziness, abdominal pain. Call your healthcare provider if you have any of these symptoms and they are severe.

Get emergency medical help if you have:

trouble breathing, shortness of breath, fast heartbeat, chest pain, swelling of your face, tongue or throat, extreme drowsiness, light-headedness when changing positions, or you are feeling faint.

These are not all the possible side effects of morphine sulfate ER tablets. Call your doctor for medical advice about side effects. You may report side effects to FDA at 1-800-FDA-1088. For more information go to dailymed.nlm.nih.gov

Manufactured for: Rhodes Pharmaceuticals L.P., Coventry, RI 02816, http://www.rhodespharma.com or call 1-888-827-0616

This Medication Guide has been approved by the U.S. Food and Drug Administration.

Revised: April 2014